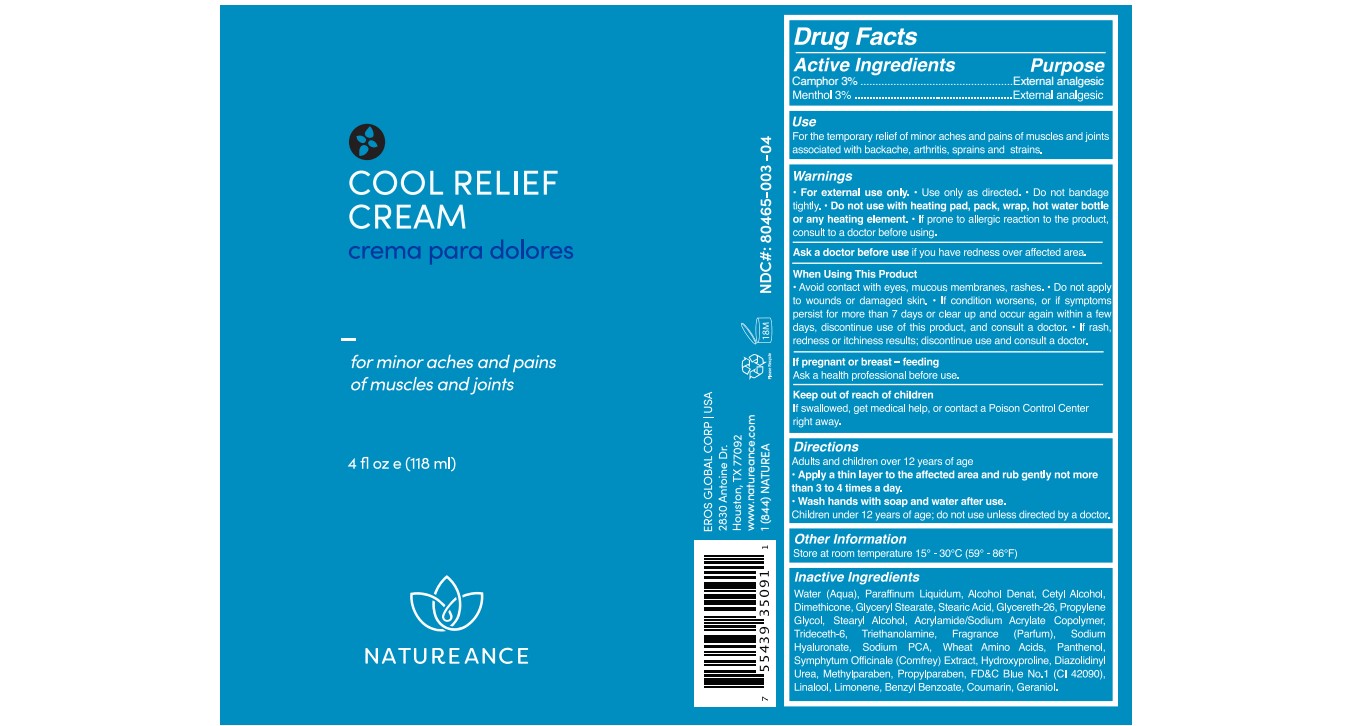 DRUG LABEL: MENTHOL, CAMPHOR
NDC: 80465-003 | Form: CREAM
Manufacturer: EROS GLOBAL
Category: otc | Type: HUMAN OTC DRUG LABEL
Date: 20240312

ACTIVE INGREDIENTS: MENTHOL 3 g/100 g; CAMPHOR (NATURAL) 3 g/100 g
INACTIVE INGREDIENTS: PROPYLENE GLYCOL; ALCOHOL; MINERAL OIL; HYALURONATE SODIUM; GERANIOL; CETYL ALCOHOL; DIMETHICONE 1000; GLYCERYL STEARATE SE; GLYCERETH-26; METHYLPARABEN; STEARYL ALCOHOL; TRIDECETH-6; PROPYLPARABEN; PANTHENOL; HYDROXYPROLINE; WATER; STEARIC ACID; DIAZOLIDINYL UREA; SODIUM PYRROLIDONE CARBOXYLATE; COMFREY; LINALOOL, (+/-)-; BENZYL BENZOATE; TROLAMINE; COUMARIN; LIMONENE, (+)-; AMINO ACIDS, WHEAT; FD&C BLUE NO. 1

80465-003-04

ACTIVE INGREDIENT

Menthol 3%

Camphor 3%

PURPOSE

External Analgesic

INDICATIONS AND USAGE

For the temporary relief of minor aches and pains of muscles and joints associated with simple backache, arthritis, sprains and strains.

WARNINGS

For external use only.
Use only as directed.
Do not bandage tightly.
Do not use with heating pad, pack, wrap, hot water bottle or any heating element.

If prone to allergic reaction to the product, consult to a doctor before using.

Ask a doctor before use if you have redness over affected area.

WHEN USING

Avoid contact with eyes, mucous membranes, rashes.
Do not apply to wounds or damaged skin.
If condition worsens, or if symptoms persist for more than 7 days or clear up and occur again within a few days, discontinue use of this product, and consult a doctor.

If rash, redness or itchiness results; discontinue use and consult a doctor.

If pregnant or breast – feeding

Ask a health professional before use.

Keep out of reach of children, if swallowed, get medical help or contact a Poison Control Center right away

DOSAGE AND ADMINISTRATION

Adults and children over 12 years of age

Apply a thin layer to the affected area and rub gently not more than 3 to 4 times a day.
Wash hands with soap and water after use.

Children under 12 years of age; do not use unless directed by a doctor.

OTHER SAFETY INFORMATION

Store at room temperature 15° - 30°C (59° - 86°F)

INACTIVE INGREDIENT

Water (Aqua), Paraffinum Liquidum, Alcohol Denat, Cetyl Alcohol, Dimethicone, Glyceryl Stearate, Stearic Acid, Glycereth-26, Propylene Glycol, Stearyl Alcohol, Acrylamide/Sodium Acrylate Copolymer, Trideceth-6, Triethanolamine, Fragrance (Parfum), Sodium Hyaluronate, Sodium PCA, Wheat Amino Acids, Panthenol, Symphytum Officinale (Comfrey) Extract, Hydroxyproline, Diazolidinyl Urea, Methylparaben, Propylparaben, FD&C Blue No.1 (CI 42090), Linalool, Limonene, Benzyl Benzoate, Coumarin, Geraniol.